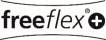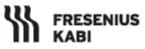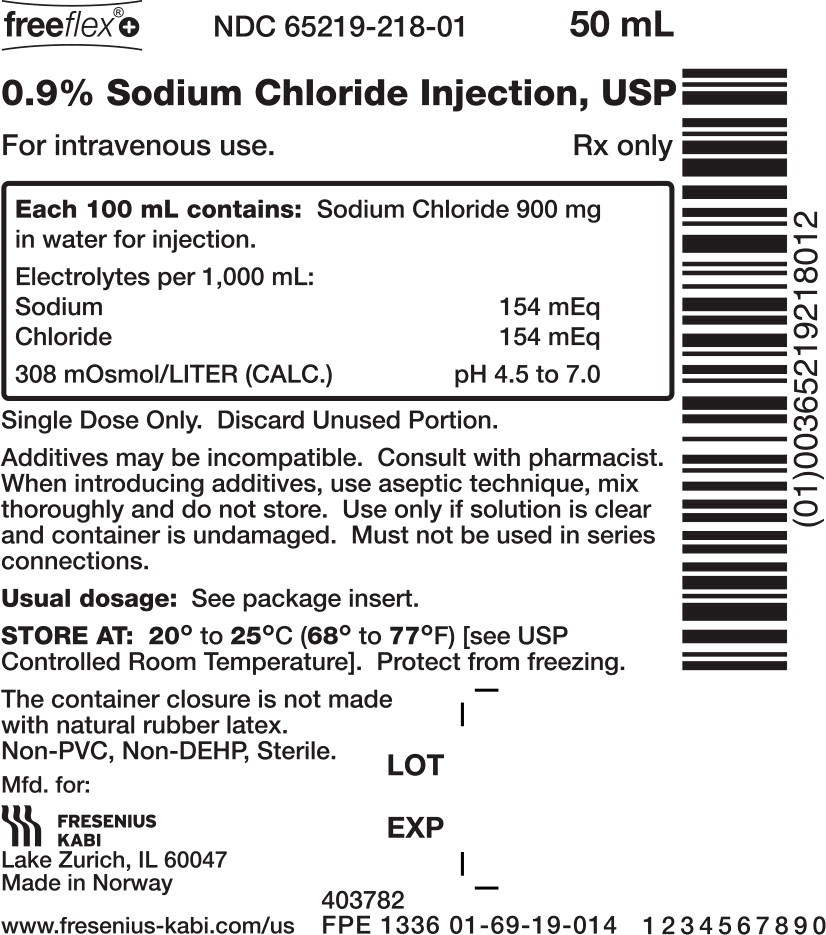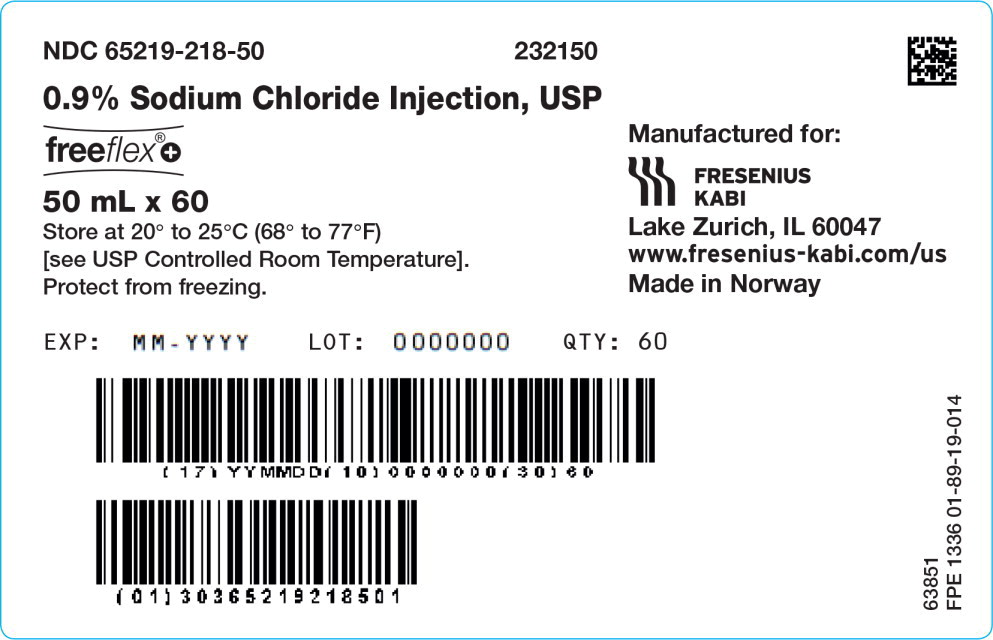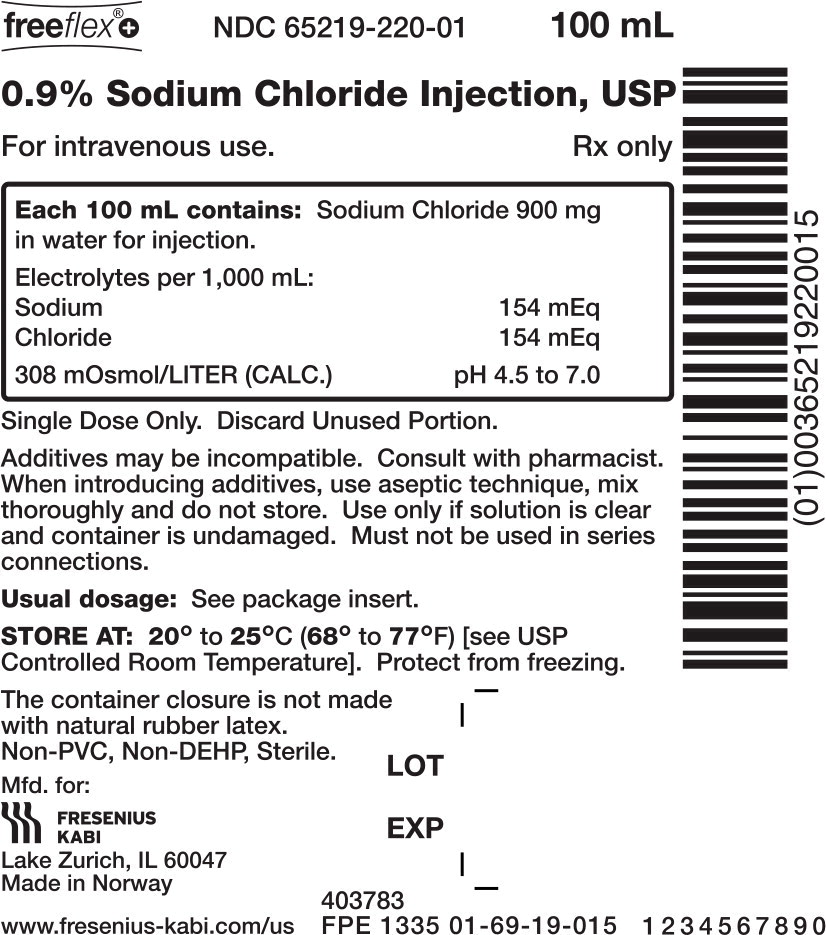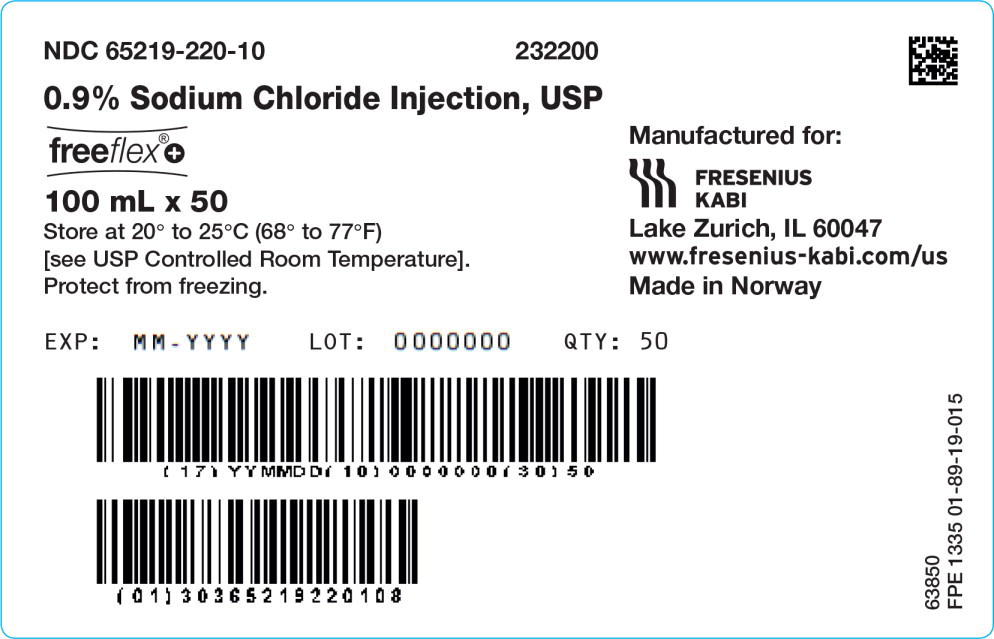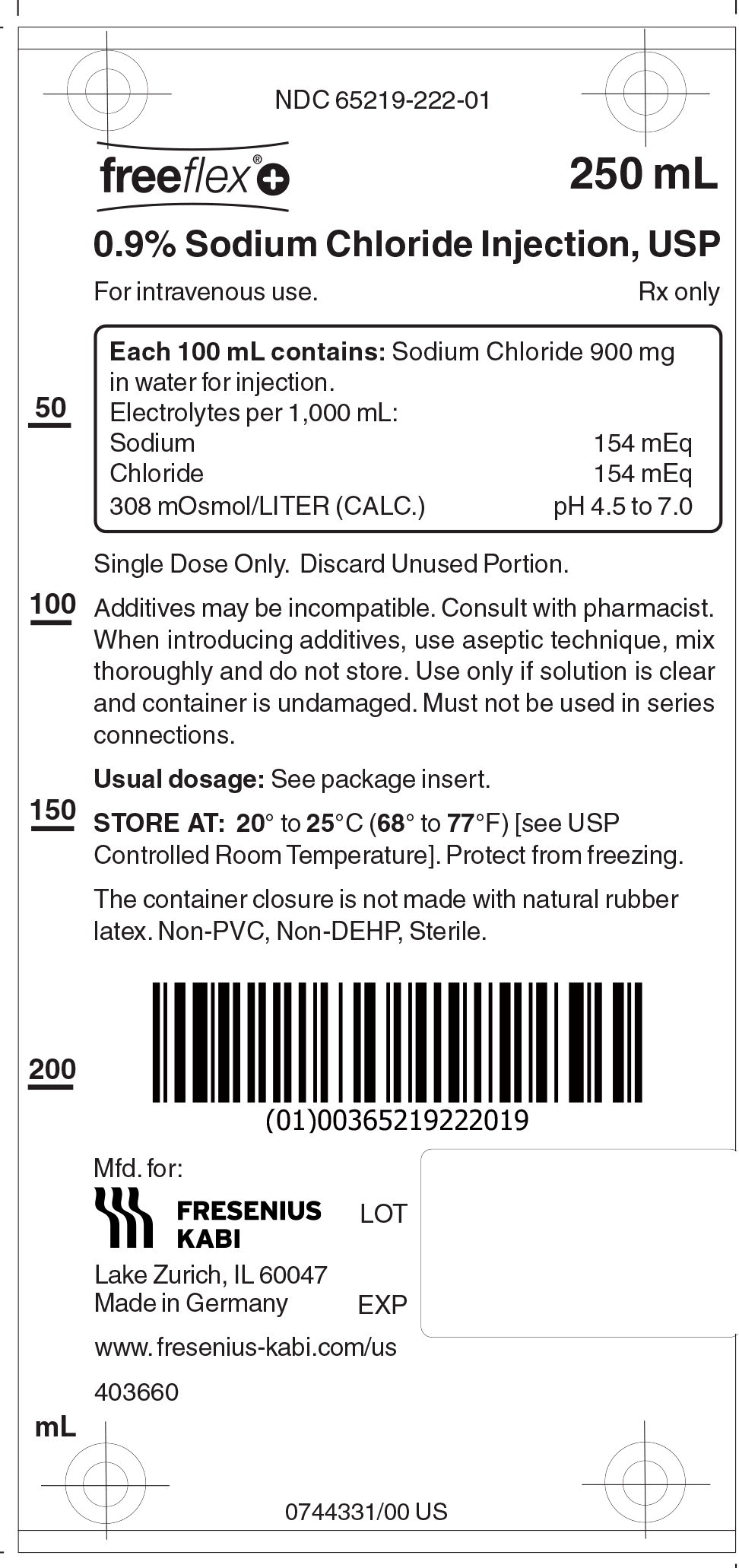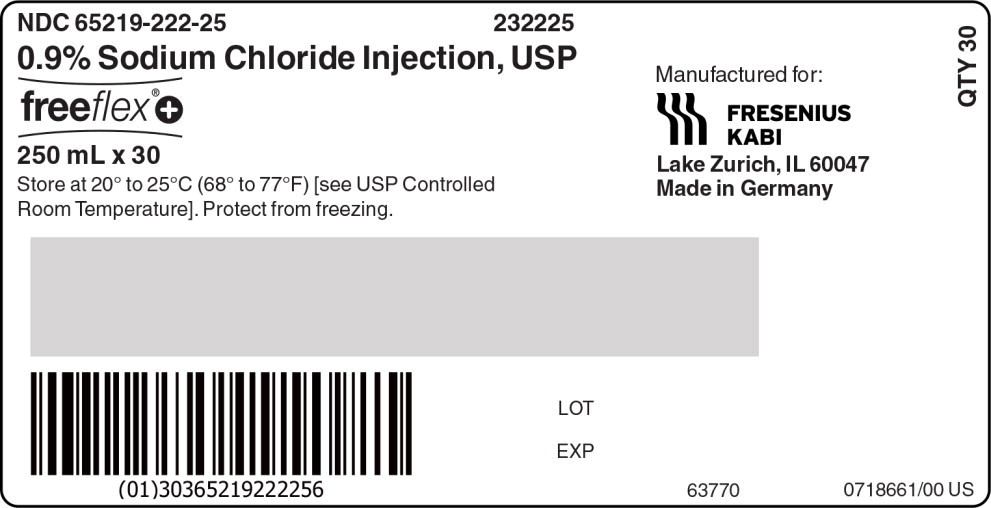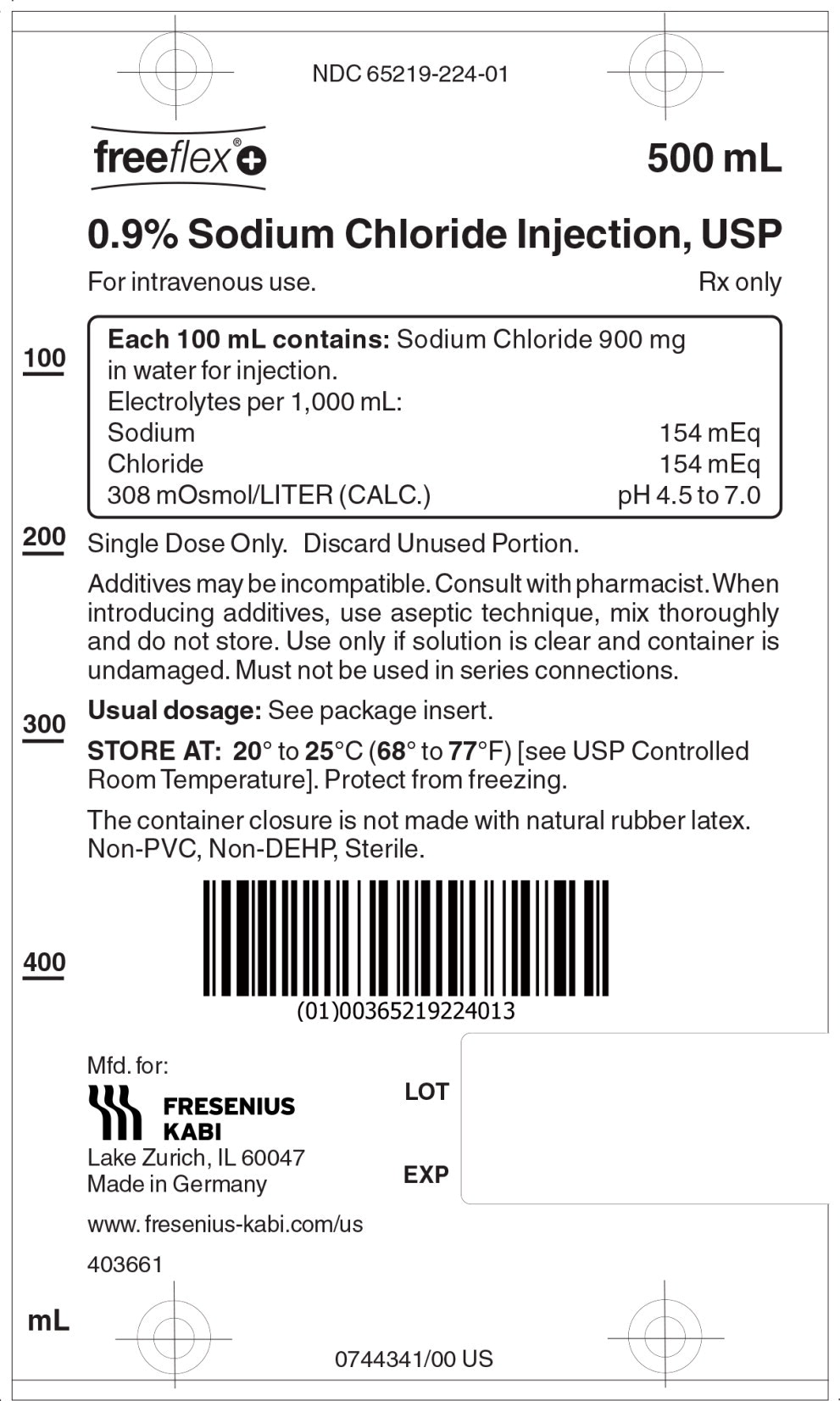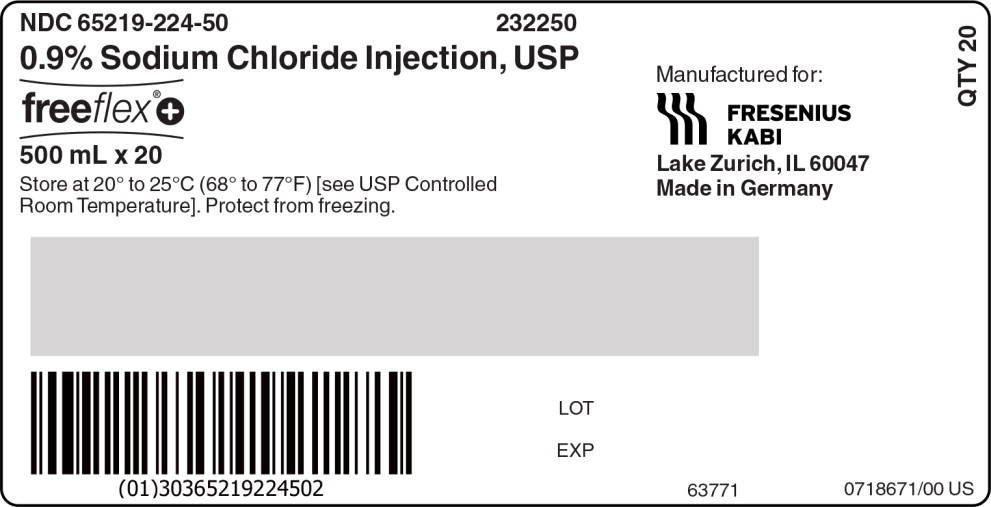 DRUG LABEL: Sodium chloride

NDC: 65219-220 | Form: INJECTION, SOLUTION
Manufacturer: Fresenius Kabi USA, LLC

Category: prescription | Type: HUMAN PRESCRIPTION DRUG LABEL
Date: 20260119

ACTIVE INGREDIENTS: SODIUM CHLORIDE
 9 mg/1 mL
INACTIVE INGREDIENTS: WATER

0.9% Sodium Chloride Injection, USP

Rx only

DESCRIPTION

0.9% Sodium Chloride Injection, USP solution is sterile and nonpyrogenic. It is a parenteral solution containing sodium chloride in water for injection intended for intravenous administration.

For 0.9% Sodium Chloride Injection, USP, each 100 mL contains 900 mg sodium chloride in water for injection. Electrolytes per 1,000 mL: sodium 154 mEq; chloride 154 mEq. The osmolarity is 308 mOsmol/L (calc.).

The pH in the 100 mL and smaller containers is 6.0; for the 250 mL and larger containers, the pH is 5.6. The pH range is 4.5 to 7.0 for all containers.

The solution contains no bacteriostat, antimicrobial agent or added buffer and is intended only as a single-dose injection. When smaller doses are required the unused portion should be discarded.

The solution is a parenteral fluid and electrolyte replenisher.

Sodium Chloride, USP is chemically designated NaCl, a white crystalline powder freely soluble in water.

Water for injection, USP is chemically designated H2O.

The flexible container is fabricated from a specially formulated non-plasticized, film containing polypropylene and thermoplastic elastomers (freeflex® bag). The freeflex®+ bag has a needle-free injection port and can accept standard luer lock syringes to add medication. The amount of water that can permeate from the container into the overwrap is insufficient to affect the solution significantly. Solutions in contact with the flexible container can leach out certain of the container's chemical components in very small amounts within the expiration period. The suitability of the container material has been confirmed by tests in animals according to USP biological tests for plastic containers.

CLINICAL PHARMACOLOGY

When administered intravenously, the solution provides a source of water and electrolytes.

Solutions which provide combinations of hypotonic or isotonic concentrations of sodium chloride are suitable for parenteral maintenance or replacement of water and electrolyte requirements.

Isotonic concentrations of sodium chloride are suitable for parenteral replacement of chloride losses that exceed or equal the sodium loss. Hypotonic concentrations of sodium chloride are suited for parenteral maintenance of water requirements when only small quantities of salt are desired. A hypertonic concentration of sodium chloride may be used to repair severe salt depletion syndrome.

Sodium chloride in water dissociates to provide sodium (Na^+) and chloride (Cl^-) ions. Sodium (Na^+) is the principal cation of the extracellular fluid and plays a large part in the therapy of fluid and electrolyte disturbances. Chloride (Cl^-) has an integral role in buffering action when oxygen and carbon dioxide exchange occurs in the red blood cells. The distribution and excretion of sodium (Na^+) and chloride (Cl^-) are largely under the control of the kidney which maintains a balance between intake and output.

Water is an essential constituent of all body tissues and accounts for approximately 70% of total body weight. Average normal adult daily requirements range from two to three liters (1.0 to 1.5 liters each for insensible water loss by perspiration and urine production).

Water balance is maintained by various regulatory mechanisms. Water distribution depends primarily on the concentration of electrolytes in the body compartments and sodium (Na^+) plays a major role in maintaining physiologic equilibrium.

INDICATIONS AND USAGE

Intravenous solutions containing sodium chloride are indicated for parenteral replenishment of fluid and sodium chloride as required by the clinical condition of the patient.

CONTRAINDICATIONS

None known.

WARNINGS

Sodium Chloride Injection, USP should be used with great care, if at all, in patients with congestive heart failure, severe renal insufficiency and in clinical states in which there exists edema with sodium retention.

The intravenous administration of Sodium Chloride Injection, USP can cause fluid and/or solute overloading resulting in dilution of serum electrolyte concentrations, overhydration, congested states or pulmonary edema.

The risk of dilutive states is inversely proportional to the electrolyte concentration of the injections. The risk of solute overload causing congested states with peripheral and pulmonary edema is directly proportional to the electrolyte concentrations of the injections.

In patients with diminished renal function, administration of Sodium Chloride Injection, USP may result in sodium retention.

PRECAUTIONS

General

Do not use plastic containers in series connections. Such use could result in air embolism due to residual air being drawn from the primary container before administration of the fluid from the secondary container is completed.

Pressurizing intravenous solutions contained in flexible plastic containers to increase flow rates can result in air embolism if the residual air in the container is not fully evacuated prior to administration.

Use of a vented intravenous administration set with the vent in the open position could result in air embolism. Vented intravenous administration sets with the vent in the open position should not be used with flexible plastic containers.

Laboratory Tests

Clinical evaluation and periodic laboratory determinations are necessary to monitor changes in fluid balance, electrolyte concentrations and acid-base balance during prolonged parenteral therapy or whenever the condition of the patient warrants such evaluation.

DRUG INTERACTIONS

Caution must be exercised in the administration of Sodium Chloride Injection, USP to patients receiving corticosteroids or corticotropin.

Carcinogenesis, Mutagenesis, Impairment of Fertility

Studies have not been performed with Sodium Chloride Injection, USP to evaluate the potential for carcinogenesis, mutagenesis or impairment of fertility.

Pregnancy:

Teratogenic Effects

Pregnancy Category C

Animal reproduction studies have not been conducted with Sodium Chloride Injection, USP. It is also not known whether Sodium Chloride Injection, USP can cause fetal harm when administered to a pregnant woman or can affect reproduction capacity. Sodium Chloride Injection, USP should be given to a pregnant woman only if clearly needed.

Labor and Delivery

Studies have not been conducted to evaluate the effects of Sodium Chloride Injection, USP on labor and delivery. Caution should be exercised when administrating this drug during labor and delivery.

Nursing Mothers

It is not known whether this drug is excreted in human milk. Because many drugs are excreted in human milk, caution should be exercised when Sodium Chloride Injection, USP is administered to a nursing mother.

Pediatric Use

The use of Sodium Chloride Injection, USP in pediatric patients is based on clinical practice.

Plasma electrolyte concentrations should be closely monitored in the pediatric population as this population may have impaired ability to regulate fluids and electrolytes.

Geriatric Use

Clinical studies of Sodium Chloride Injection, USP did not include sufficient numbers of subjects aged 65 and over to determine whether they respond differently from younger subjects. Other reported clinical experience has not identified differences in responses between elderly and younger patients. In general, dose selection for an elderly patient should be cautious, usually starting at the low end of the dosing range, reflecting the greater frequency of decreased hepatic, renal, or cardiac function, and of concomitant disease or drug therapy.

This drug is known to be substantially excreted by the kidney, and the risk of toxic reactions to this drug may be greater in patients with impaired renal function. Because elderly patients are more likely to have decreased renal function, care should be taken in dose selection, and it may be useful to monitor renal function.

Do not administer unless solution is clear and container is undamaged. Discard unused portion.

ADVERSE REACTIONS

Reactions which may occur because of the solution or the technique of administration include febrile response, infection at the site of injection, venous thrombosis or phlebitis extending from the site of injection, extravasation and hypervolemia.

If an adverse reaction does occur, discontinue the infusion, evaluate the patient, institute appropriate therapeutic countermeasures and save the remainder of the fluid for examination if deemed necessary.

To report SUSPECTED ADVERSE REACTIONS, contact Fresenius Kabi USA, LLC at 1-800-551-7176 or FDA at 1-800-FDA-1088 or www.fda.gov/medwatch.

OVERDOSAGE

In the event of overhydration or solute overload, re-evaluate the patient and institute appropriate corrective measures (see WARNINGS, PRECAUTIONS, and ADVERSE REACTIONS).

DOSAGE AND ADMINISTRATION

The dose is dependent upon the age, weight and clinical condition of the patient.

Additives may be incompatible. Consult with pharmacist, if available. When introducing additives, use aseptic technique, mix thoroughly and do not store.

Parenteral drug products should be inspected visually for particulate matter and discoloration prior to administration, whenever solution and container permit (see PRECAUTIONS).

INSTRUCTIONS FOR USE

Check flexible container solution composition, lot number, and expiry date.

Do not remove solution container from its overwrap until immediately before use.

Use sterile equipment and aseptic technique.

To Open

1. Turn solution container over so that the text is face down. Using the pre-cut corner tabs, peel open the overwrap and remove solution container.
2. Check the solution container for leaks by squeezing firmly. If leaks are found, or if the seal is not intact, discard the solution.
3. Do not use if the solution is cloudy or a precipitate is present.

To Add Medication

The Additive port of the freeflex®+ container accepts standard luer lock syringes. Do not use a needle for additions.

1. Identify LIGHT BLUE Additive Port with arrow pointing toward solution container.
2. Immediately before injecting additives, break off LIGHT BLUE Additive Port Cap with the arrow pointing toward solution container.
3. Hold base of LIGHT BLUE Additive Port.
4. Attach Luer Lock syringe to the threaded LIGHT BLUE Additive Port. Inject additive.
5. Mix solution container contents thoroughly.

Preparation for Administration

1. Immediately before inserting the infusion set, break off BLUE Infusion Port Cap with the arrow pointing away from container.
2. Use a non-vented infusion set or close the air-inlet on a vented set.
3. Close the roller clamp of the infusion set.
4. Hold the base of BLUE Infusion Port.
5. Insert spike through BLUE Infusion Port by rotating wrist slightly until the spike is inserted.
  NOTE: See full directions accompanying administration set.

WARNING: Do not use flexible container in series connections.

HOW SUPPLIED

0.9% Sodium Chloride Injection, USP is supplied in single-dose flexible plastic containers as follows:

Product Code | Unit of Sale | Strength | Each
232150 | NDC 65219-218-50 Package of 60 freeflex®+ bags | 0.9% (450 mg per 50 mL) (9 mg/mL) | NDC 65219-218-01 50 mL in a 100 mL freeflex®+ bag
232200 | NDC 65219-220-10 Package of 50 freeflex®+ bags | 0.9% (900 mg per 100 mL) (9 mg/mL) | NDC 65219-220-01 100 mL freeflex®+ bag
232225 | 65219-222-25 Package of 30 freeflex®+ bags | 0.9% (2,250 mg per 250 mL) (9 mg/mL) | 65219-222-01 250 mL freeflex® + bag
232250 | 65219-224-50 Package of 20 freeflex®+ bags | 0.9% (4,500 mg per 500 mL) (9 mg/mL) | 65219-224-01 500 mL freeflex® + bag

Store at 20° to 25°C (68° to 77°F) [see USP Controlled Room Temperature]. Protect from freezing. The container closure is not made with natural rubber latex. Non-PVC, Non-DEHP, Sterile.

Lake Zurich, IL 60047

www.fresenius-kabi.com/us

Revised: July 2024

PACKAGE LABEL

PACKAGE LABEL - PRINCIPAL DISPLAY – 0.9% Sodium Chloride 50 mL Bag Label

freeflex®+ NDC 65219-218-01 50 mL
0.9% Sodium Chloride Injection, USP

For intravenous use. Rx only

PACKAGE LABEL

PACKAGE LABEL - PRINCIPAL DISPLAY – 0.9% Sodium Chloride 50 mL Case Label

NDC 65219-218-50 232150

0.9% Sodium Chloride Injection, USP

freeflex®+

50 mL x 60

Store at 20° to 25°C (68° to 77°F)

[see USP Controlled Room Temperature].

Protect from freezing.

PACKAGE LABEL

PACKAGE LABEL - PRINCIPAL DISPLAY – 0.9% Sodium Chloride 100 mL Bag Label

freeflex®+ NDC 65219-220-01 100 mL
0.9% Sodium Chloride Injection, USP

For intravenous use. Rx only

PACKAGE LABEL

PACKAGE LABEL - PRINCIPAL DISPLAY – 0.9% Sodium Chloride 100 mL Case Label

NDC 65219-220-10 232200

0.9% Sodium Chloride Injection, USP

freeflex®+

100 mL x 50

Store at 20° to 25°C (68° to 77°F)

[see USP Controlled Room Temperature].

Protect from freezing.

PACKAGE LABEL

PACKAGE LABEL - PRINCIPAL DISPLAY – 0.9% Sodium Chloride 250 mL Bag Label

NDC 65219-222-01

freeflex®+ 250 mL
0.9% Sodium Chloride Injection, USP

For intravenous use. Rx only

PACKAGE LABEL

PACKAGE LABEL - PRINCIPAL DISPLAY – 0.9% Sodium Chloride 250 mL Case Label

NDC 65219-222-25 232225

0.9% Sodium Chloride Injection, USP

freeflex®+

250 mL x 30

Store at 20° to 25°C (68° to 77°F)

[see USP Controlled Room Temperature].

Protect from freezing.

PACKAGE LABEL

PACKAGE LABEL - PRINCIPAL DISPLAY – 0.9% Sodium Chloride 500 mL Bag Label

NDC 65219-224-01

freeflex®+ 500 mL
0.9% Sodium Chloride Injection, USP

For intravenous use. Rx only

PACKAGE LABEL

PACKAGE LABEL - PRINCIPAL DISPLAY – 0.9% Sodium Chloride 500 mL Case Label

NDC 65219-224-50 232250

0.9% Sodium Chloride Injection, USP

freeflex®+

500 mL x 20

Store at 20° to 25°C (68° to 77°F)

[see USP Controlled Room Temperature].

Protect from freezing.